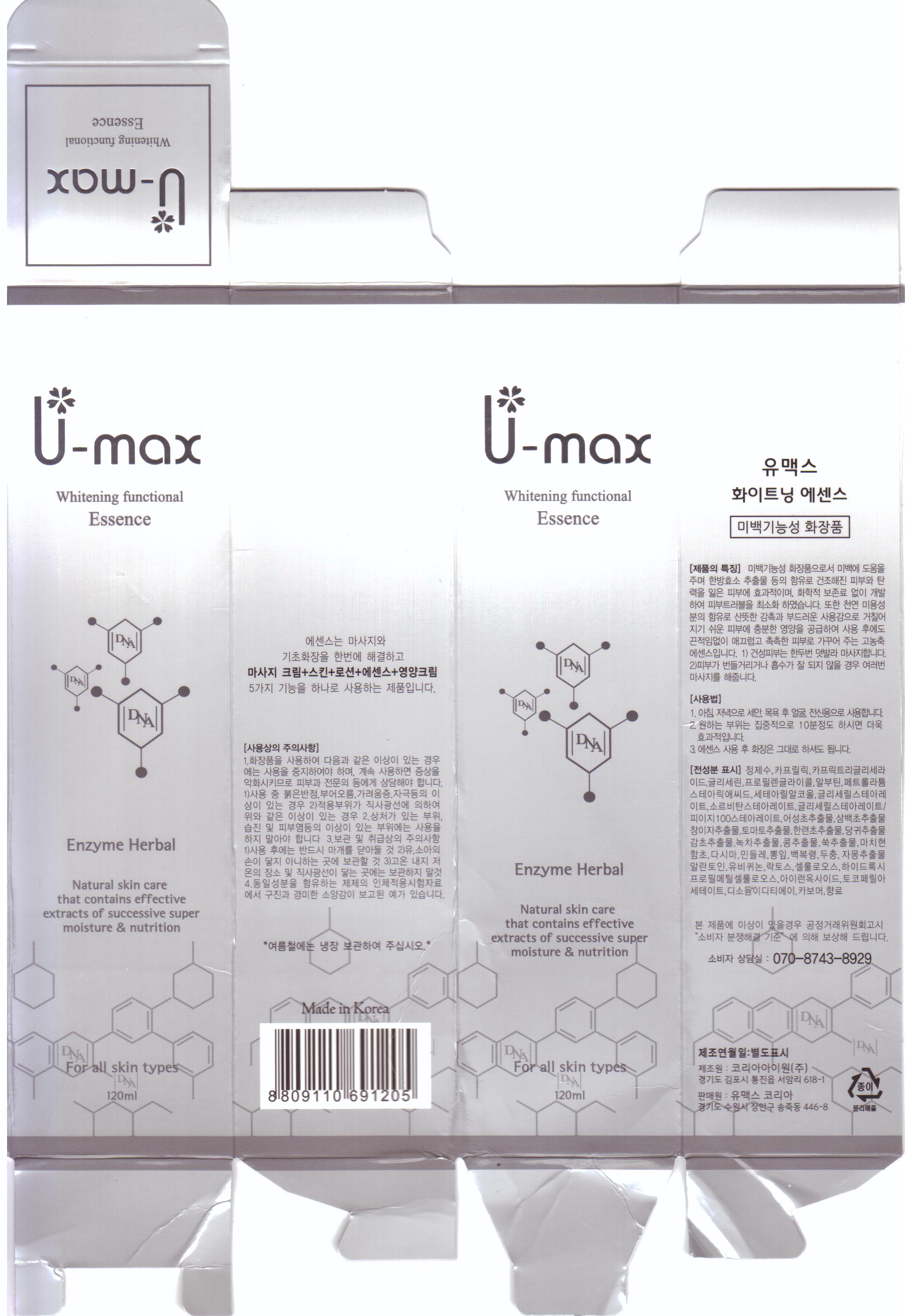 DRUG LABEL: U-max Whitening Functional Essence
NDC: 50795-3001 | Form: CREAM
Manufacturer: VS Shinbi Co., Ltd.
Category: otc | Type: HUMAN OTC DRUG LABEL
Date: 20120604

ACTIVE INGREDIENTS: ALLANTOIN 0.1 mL/100 mL
INACTIVE INGREDIENTS: WATER; GLYCERIN; PROPYLENE GLYCOL; HOUTTUYNIA CORDATA FLOWERING TOP; XANTHIUM STRUMARIUM FRUIT; SOLANUM LYCOPERSICUM; ANGELICA GIGAS ROOT; GLYCYRRHIZA GLABRA; ARTEMISIA VULGARIS ROOT; ARBUTIN; .ALPHA.-TOCOPHEROL ACETATE; MINERAL OIL; STEARIC ACID; CETOSTEARYL ALCOHOL; LAMINARIA JAPONICA; TARAXACUM OFFICINALE; CITRUS PARADISI SEED; GLYCERYL MONOSTEARATE; SORBITAN SESQUIOLEATE; GREEN TEA LEAF; PORTULACA OLERACEA WHOLE; SALICORNIA EUROPAEA

Drug Facts

active ingredient: allantoin

inactive ingredient: water, glycerin, propylene glycol, arbutin, disodium EDTA, tocopheryl acetate, carbomer, caprylic triglyceride, petrolatum, stearic acid, cetearyl alcohol, glyceryl stearate, sorbitan stearate, houttuynia cordata extract, saururus chinensis extract, xanthium strumarium fruit extract, solanum lycopersicum fruit extract, eclipta prostrata leaf extract, angelica gigas root extract, glycyrrhiza glabra root extract, camellia sinensis leaf extract, hydrolyzed soybean extract, artemisia vulgaris extract, perfume, portulaca oleracea extract, salicornia herbacea extract, laminaria japonica extract, taraxacum officinale leaf extract, morus bombycis leaf extract, poria cocos extract, eucommia ulmoides leaf extract, citrus paradisi seed oil, ubiquinone, biosaccharide gum-1, hydroxypropyl methylcellulose, iron titanium oxide, cellulose

PURPOSE

skin whitening

keep out of reach of the children

INDICATIONS AND USAGE

- apply only for skin
- apply 2 or 3 times a day with 5~6ml
- massage with your finger over 2 min and let them dry

WARNINGS

- keep out of eyes, ears and mouth
- if contact occurs, rinse away with plenty of cold water

DOSAGE AND ADMINISTRATION

- for external use only